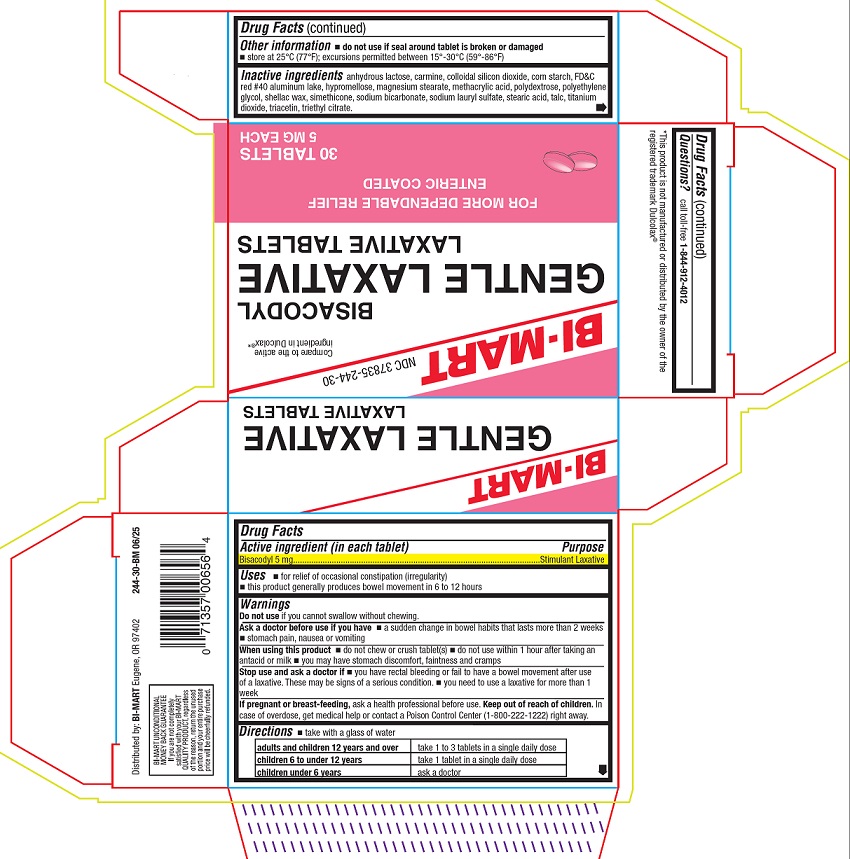 DRUG LABEL: Gentle Laxative
NDC: 37835-244 | Form: TABLET, DELAYED RELEASE
Manufacturer: Bi-Mart
Category: otc | Type: HUMAN OTC DRUG LABEL
Date: 20250821

ACTIVE INGREDIENTS: BISACODYL 5 mg/1 1
INACTIVE INGREDIENTS: SILICON DIOXIDE; STARCH, CORN; FD&C RED NO. 40 ALUMINUM LAKE; HYPROMELLOSE, UNSPECIFIED; ANHYDROUS LACTOSE; MAGNESIUM STEARATE; METHACRYLIC ACID; POLYDEXTROSE; POLYETHYLENE GLYCOL, UNSPECIFIED; SHELLAC; DIMETHICONE; SODIUM BICARBONATE; SODIUM LAURYL SULFATE; STEARIC ACID; TALC; TITANIUM DIOXIDE; TRIACETIN; TRIETHYL CITRATE

Active ingredient (in each tablet)

Bisacodyl 5 mg

Purpose

Stimulant laxative

Uses

- for relief of occasional constipation (irregularity)
- this product generally produces bowel movement in 6 to 12 hours

Warnings

Do not use

if you cannot swallow without chewing.

Ask a doctor before use if you have

- a sudden change in bowel habits that lasts more than 2 weeks
- stomach pain, nausea or vomiting

When using this product

- do not chew or crush tablet(s)
- do not use within 1 hour after taking an antacid or milk
- you may have stomach discomfort, faintness, and cramps

Stop use and ask a doctor if

- you have rectal bleeding or fail to have a bowel movement after use of a laxative. These may be signs of a serious condition.
- you need to use a laxative for more than 1 week

If pregnant or breast-feeding,

ask a health professional before use.

Keep out of reach of children.

In case of overdose, get medical help or contact a Poison Control Center (1-800-222-1222) right away.

Directions

- take with a glass of water

adults and children 12 years and over | take 1 to 3 tablets in a single daily dose
children 6 to under 12 years | take 1 tablet in a single daily dose
children under 6 years | ask a doctor

Other information

- do not use if seal around tablet is broken or damaged
- store at 25°C (77°F); excursions permitted between 15°-30°C (59°-86°F)

Inactive ingredients

anhydrous lactose, carmine, colloidal silicon dioxide, corn starch, FD&C red #40 aluminum lake, hypromellose, magnesium stearate, methacrylic acid, polydextrose, polyethylene glycol, shellac wax, simethicone, sodium bicarbonate, sodium lauryl sulfate, stearic acid, talc, titanium dioxide, triacetin, triethyl citrate.

Questions?

call toll-free 1-844-912-4012